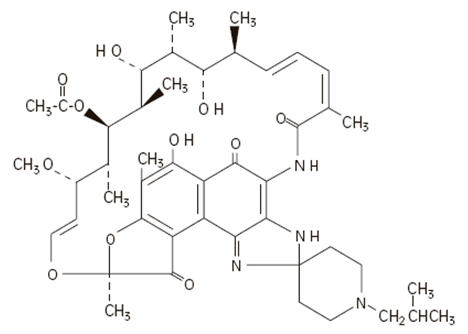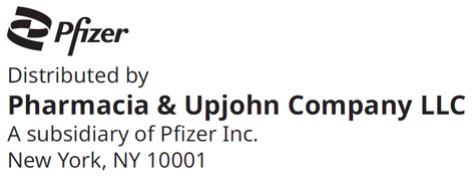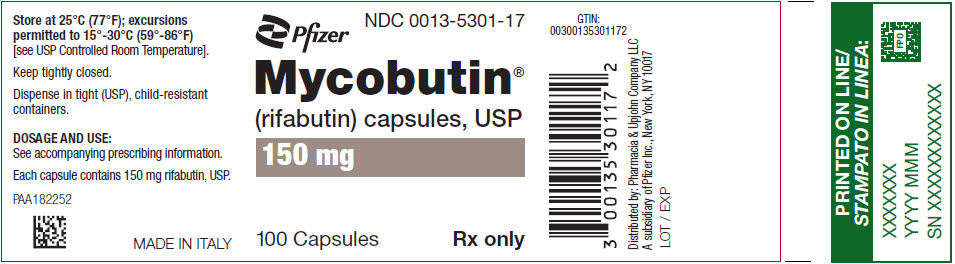 DRUG LABEL: Mycobutin
NDC: 0013-5301 | Form: CAPSULE
Manufacturer: Pfizer Laboratories Div Pfizer Inc
Category: prescription | Type: HUMAN PRESCRIPTION DRUG LABEL
Date: 20241224

ACTIVE INGREDIENTS: RIFABUTIN 150 mg/1 1
INACTIVE INGREDIENTS: MICROCRYSTALLINE CELLULOSE; MAGNESIUM STEARATE; FERRIC OXIDE RED; SILICON DIOXIDE; SODIUM LAURYL SULFATE; TITANIUM DIOXIDE

Mycobutin®
(Rifabutin) Capsules, USP

DESCRIPTION

MYCOBUTIN Capsules for oral administration contain 150 mg of the rifamycin antimycobacterial agent rifabutin, USP, per capsule, along with the inactive ingredients, microcrystalline cellulose, magnesium stearate, red iron oxide, silica gel, sodium lauryl sulfate, titanium dioxide, and edible white ink.

The chemical name for rifabutin is 1',4-didehydro-1-deoxy-1,4-dihydro-5'-(2-methylpropyl)-1-oxorifamycin XIV (Chemical Abstracts Service, 9th Collective Index) or (9S,12E,14S,15R, 16S,17R,18R,19R,20S,21S,22E, 24Z)-6,16,18,20-tetrahydroxy-1'-isobutyl-14-methoxy-7,9,15,17,19,21,25-heptamethyl-spiro [9,4-(epoxypentadeca[1,11,13]trienimino)-2H-furo[2',3':7,8]naphth[1,2-d] imidazole-2,4'-piperidine]-5,10,26-(3H,9H)-trione-16-acetate. Rifabutin has a molecular formula of C46H62N4O11, a molecular weight of 847.02 and the following structure:

Rifabutin is a red-violet powder soluble in chloroform and methanol, sparingly soluble in ethanol, and very slightly soluble in water (0.19 mg/mL). Its log P value (the base 10 logarithm of the partition coefficient between n-octanol and water) is 3.2 (n-octanol/water).

CLINICAL PHARMACOLOGY

Pharmacokinetics

Absorption

Following a single oral dose of 300 mg to nine healthy adult volunteers, rifabutin was readily absorbed from the gastrointestinal tract with mean (±SD) peak plasma levels (Cmax) of 375 (±267) ng/mL (range: 141 to 1033 ng/mL) attained in 3.3 (±0.9) hours (Tmax range: 2 to 4 hours). Absolute bioavailability assessed in five HIV-positive patients, who received both oral and intravenous doses, averaged 20%. Total recovery of radioactivity in the urine indicates that at least 53% of the orally administered rifabutin dose is absorbed from the gastrointestinal tract. The bioavailability of rifabutin from the capsule dosage form, relative to an oral solution, was 85% in 12 healthy adult volunteers. High-fat meals slow the rate without influencing the extent of absorption from the capsule dosage form. Plasma concentrations post-Cmax declined in an apparent biphasic manner. Pharmacokinetic dose-proportionality was established over the 300 mg to 600 mg dose range in nine healthy adult volunteers (crossover design) and in 16 early symptomatic human immunodeficiency virus (HIV)-positive patients over a 300 mg to 900 mg dose range.

Distribution

Due to its high lipophilicity, rifabutin demonstrates a high propensity for distribution and intracellular tissue uptake. Following intravenous dosing, estimates of apparent steady-state distribution volume (9.3 ± 1.5 L/kg) in five HIV-positive patients exceeded total body water by approximately 15-fold. Substantially higher intracellular tissue levels than those seen in plasma have been observed in both rat and man. The lung-to-plasma concentration ratio, obtained at 12 hours, was approximately 6.5 in four surgical patients who received an oral dose. Mean rifabutin steady-state trough levels (Cp,minss; 24-hour post-dose) ranged from 50 to 65 ng/mL in HIV-positive patients and in healthy adult volunteers. About 85% of the drug is bound in a concentration-independent manner to plasma proteins over a concentration range of 0.05 to 1 µg/mL. Binding does not appear to be influenced by renal or hepatic dysfunction. Rifabutin was slowly eliminated from plasma in seven healthy adult volunteers, presumably because of distribution-limited elimination, with a mean terminal half-life of 45 (±17) hours (range: 16 to 69 hours). Although the systemic levels of rifabutin following multiple dosing decreased by 38%, its terminal half-life remained unchanged.

Metabolism

Of the five metabolites that have been identified, 25-O-desacetyl and 31-hydroxy are the most predominant, and show a plasma metabolite:parent area under the curve ratio of 0.10 and 0.07, respectively. The former has an activity equal to the parent drug and contributes up to 10% to the total antimicrobial activity.

Excretion

A mass-balance study in three healthy adult volunteers with ^14C-labeled rifabutin showed that 53% of the oral dose was excreted in the urine, primarily as metabolites. About 30% of the dose is excreted in the feces. Mean systemic clearance (CLs/F) in healthy adult volunteers following a single oral dose was 0.69 (±0.32) L/hr/kg (range: 0.46 to 1.34 L/hr/kg). Renal and biliary clearance of unchanged drug each contribute approximately 5% to CLs/F.

Pharmacokinetics in Special Populations

Geriatric

Compared to healthy volunteers, steady-state pharmacokinetics of MYCOBUTIN are more variable in elderly patients (>70 years).

Pediatric

The pharmacokinetics of MYCOBUTIN have not been studied in subjects under 18 years of age.

Renal Impairment

The disposition of rifabutin (300 mg) was studied in 18 patients with varying degrees of renal function. Area under plasma concentration time curve (AUC) increased by about 71% in patients with severe renal impairment (creatinine clearance below 30 mL/min) compared to patients with creatinine clearance (Crcl) between 61–74 mL/min. In patients with mild to moderate renal impairment (Crcl between 30–61 mL/min), the AUC increased by about 41%. In patients with severe renal impairment, carefully monitor for rifabutin associated adverse events. A reduction in the dosage of rifabutin is recommended for patients with Crcl <30 mL/min if toxicity is suspected (see DOSAGE AND ADMINISTRATION).

Hepatic Impairment

Mild hepatic impairment does not require a dose modification. The pharmacokinetics of rifabutin in patients with moderate and severe hepatic impairment is not known.

Malabsorption in HIV-Infected Patients

Alterations in gastric pH due to progressing HIV disease has been linked with malabsorption of some drugs used in HIV-positive patients (e.g., rifampin, isoniazid). Drug serum concentrations data from AIDS patients with varying disease severity (based on CD4+ counts) suggests that rifabutin absorption is not influenced by progressing HIV disease.

Drug-Drug Interactions

(see also PRECAUTIONS-Drug Interactions)

Multiple dosing of rifabutin has been associated with induction of hepatic metabolic enzymes of the CYP3A subfamily. Rifabutin's predominant metabolite (25-desacetyl rifabutin: LM565), may also contribute to this effect. Metabolic induction due to rifabutin is likely to produce a decrease in plasma concentrations of concomitantly administered drugs that are primarily metabolized by the CYP3A enzymes. Similarly concomitant medications that competitively inhibit the CYP3A activity may increase plasma concentrations of rifabutin.

CLINICAL STUDIES

Two randomized, double-blind clinical trials (Study 023 and Study 027) compared MYCOBUTIN (300 mg/day) to placebo in patients with CDC-defined AIDS and CD4 counts ≤200 cells/µL. These studies accrued patients from 2/90 through 2/92. Study 023 enrolled 590 patients, with a median CD4 cell count at study entry of 42 cells/µL (mean 61). Study 027 enrolled 556 patients with a median CD4 cell count at study entry of 40 cells/µL (mean 58).

Endpoints included the following:

- MAC bacteremia, defined as at least one blood culture positive for Mycobacterium avium complex (MAC) bacteria.
- Clinically significant disseminated MAC disease, defined as MAC bacteremia accompanied by signs or symptoms of serious MAC infection, including one or more of the following: fever, night sweats, rigors, weight loss, worsening anemia, and/or elevations in alkaline phosphatase.
- Survival.

MAC Bacteremia

Participants who received MYCOBUTIN were one-third to one-half as likely to develop MAC bacteremia as were participants who received placebo. These results were statistically significant (Study 023: p<0.001; Study 027: p = 0.002).

In Study 023, the one-year cumulative incidence of MAC bacteremia, on an intent to treat basis, was 9% for patients randomized to MYCOBUTIN and 22% for patients randomized to placebo. In Study 027, these rates were 13% and 28% for patients receiving MYCOBUTIN and placebo, respectively.

Most cases of MAC bacteremia (approximately 90% in these studies) occurred among participants whose CD4 count at study entry was ≤100 cells/µL. The median and mean CD4 counts at onset of MAC bacteremia were 13 cells/µL and 24 cells/µL, respectively. These studies did not investigate the optimal time to begin MAC prophylaxis.

Clinically Significant Disseminated MAC Disease

In association with the decreased incidence of bacteremia, patients on MYCOBUTIN showed reductions in the signs and symptoms of disseminated MAC disease, including fever, night sweats, weight loss, fatigue, abdominal pain, anemia, and hepatic dysfunction.

Survival

The one-year survival rates in Study 023 were 77% for the group receiving MYCOBUTIN and 77% for the placebo group. In Study 027, the one-year survival rates were 77% for the group receiving MYCOBUTIN and 70% for the placebo group.

These differences were not statistically significant.

Microbiology

Mechanism of Action

Rifabutin inhibits DNA-dependent RNA polymerase in susceptible strains of Escherichia coli and Bacillus subtilis but not in mammalian cells. In resistant strains of E. coli, rifabutin, like rifampin, did not inhibit this enzyme. It is not known whether rifabutin inhibits DNA-dependent RNA polymerase in Mycobacterium avium or in M. intracellulare which comprise M. avium complex (MAC).

Susceptibility Testing

For specific information regarding susceptibility test interpretive criteria and associated test methods and quality control standards recognized by FDA for this drug, please see: https://www.fda.gov/STIC.

In Vitro Studies

Rifabutin has demonstrated in vitro activity against M. avium complex (MAC) organisms isolated from both HIV-positive and HIV-negative people. While-gene probe techniques may be used to identify these two organisms, many reported studies did not distinguish between these two species. The vast majority of isolates from MAC-infected, HIV-positive people are M. avium, whereas in HIV-negative people, about 40% of the MAC isolates are M. intracellulare.

Various in vitro methodologies employing broth or solid media, with and without polysorbate 80 (Tween 80), have been used to determine rifabutin MIC values for mycobacterial species. In general, MIC values determined in broth are several fold lower than that observed with methods employing solid media. Utilization of Tween 80 in these assays has been shown to further lower MIC values.

However, MIC values were substantially higher for egg-based compared to agar-based solid media.

Rifabutin activity against 211 MAC isolates from HIV-positive people was evaluated in vitro utilizing a radiometric broth and an agar dilution method. Results showed that 78% and 82% of these isolates had MIC99 values of ≤0.25 µg/mL and ≤1.0 µg/mL, respectively, when evaluated by these two methods. Rifabutin was also shown to be active against phagocytized, M. avium complex in a mouse macrophage cell culture model.

Rifabutin has in vitro activity against many strains of Mycobacterium tuberculosis. In one study, utilizing the radiometric broth method, each of 17 and 20 rifampin-naive clinical isolates tested from the United States and Taiwan, respectively, were shown to be susceptible to rifabutin concentrations of ≤0.125 µg/mL.

Cross-resistance between rifampin and rifabutin is commonly observed with M. tuberculosis and M. avium complex isolates. Isolates of M. tuberculosis resistant to rifampin are likely to be resistant to rifabutin. Rifampicin and rifabutin MIC99 values against 523 isolates of M. avium complex were determined utilizing the agar dilution method (Heifets, Leonid B. and Iseman, Michael D. Determination of in vitro susceptibility of Mycobacteria to Ansamycin. Am. Rev. Respir. Dis. 1985; 132(3):710–711).

Table 1 Susceptibility of M. Avium Complex Strains to Rifampin and Rifabutin

 |  | % of Strains Susceptible/Resistant to Different Concentrations of Rifabutin (μg/mL)
Susceptibility to Rifampin (µg/mL) | Number of Strains | Susceptible to 0.5 | Resistant to 0.5 only | Resistant to 1.0 | Resistant to 2.0
Susceptible to 1.0 | 30 | 100.0 | 0.0 | 0.0 | 0.0
Resistant to 1.0 only | 163 | 88.3 | 11.7 | 0.0 | 0.0
Resistant to 5.0 | 105 | 38.0 | 57.1 | 2.9 | 2.0
Resistant to 10.0 | 225 | 20.0 | 50.2 | 19.6 | 10.2
TOTAL | 523 | 49.5 | 36.7 | 9.0 | 4.8

Rifabutin in vitro MIC99 values of ≤0.5 µg/mL, determined by the agar dilution method, for M. kansasii, M. gordonae and M. marinum have been reported; however, the clinical significance of these results is unknown.

INDICATIONS AND USAGE

MYCOBUTIN Capsules are indicated for the prevention of disseminated Mycobacterium avium complex (MAC) disease in patients with advanced HIV infection.

CONTRAINDICATIONS

MYCOBUTIN Capsules are contraindicated in patients who have had clinically significant hypersensitivity to rifabutin or to any other rifamycins.

MYCOBUTIN Capsules are contraindicated in patients being treated with cabotegravir/rilpivirine prolonged-release injectable suspension (see PRECAUTIONS-Drug Interactions, Table 2).

WARNINGS

Tuberculosis

MYCOBUTIN Capsules must not be administered for MAC prophylaxis to patients with active tuberculosis. Patients who develop complaints consistent with active tuberculosis while on prophylaxis with MYCOBUTIN should be evaluated immediately, so that those with active disease may be given an effective combination regimen of anti-tuberculosis medications. Administration of MYCOBUTIN as a single agent to patients with active tuberculosis is likely to lead to the development of tuberculosis that is resistant both to MYCOBUTIN and to rifampin.

There is no evidence that MYCOBUTIN is an effective prophylaxis against M. tuberculosis. Patients requiring prophylaxis against both M. tuberculosis and Mycobacterium avium complex may be given isoniazid and MYCOBUTIN concurrently.

Tuberculosis in HIV-positive patients is common and may present with atypical or extrapulmonary findings. Patients are likely to have a nonreactive purified protein derivative (PPD) despite active disease. In addition to chest X-ray and sputum culture, the following studies may be useful in the diagnosis of tuberculosis in the HIV-positive patient: blood culture, urine culture, or biopsy of a suspicious lymph node.

MAC Treatment with Clarithromycin

When MYCOBUTIN is used concomitantly with clarithromycin for MAC treatment, a decreased dose of MYCOBUTIN is recommended due to the increase in plasma concentrations of MYCOBUTIN (see PRECAUTIONS-Drug Interactions, Table 2).

Hypersensitivity and Related Reactions

Hypersensitivity reactions may occur in patients receiving rifamycins. Signs and symptoms of these reactions may include hypotension, urticaria, angioedema, acute bronchospasm, conjunctivitis, thrombocytopenia, neutropenia or flu-like syndrome (weakness, fatigue, muscle pain, nausea, vomiting, headache, fever, chills, aches, rash, itching, sweats, dizziness, shortness of breath, chest pain, cough, syncope, palpitations). There have been reports of anaphylaxis with the use of rifamycins.

Monitor patients receiving MYCOBUTIN therapy for signs and/or symptoms of hypersensitivity reactions. If these symptoms occur, administer supportive measures and discontinue MYCOBUTIN.

Uveitis

Due to the possible occurrence of uveitis, patients should also be carefully monitored when MYCOBUTIN is given in combination with clarithromycin (or other macrolides) and/or fluconazole and related compounds (see PRECAUTIONS-Drug Interactions, Table 2). If uveitis is suspected, the patient should be referred to an ophthalmologist and, if considered necessary, treatment with MYCOBUTIN should be suspended (see also ADVERSE REACTIONS).

Clostridioides difficile associated diarrhea (CDAD) has been reported with use of nearly all antibacterial agents, including MYCOBUTIN (rifabutin) Capsules, USP, and may range in severity from mild diarrhea to fatal colitis. Treatment with antibacterial agents alters the normal flora of the colon leading to overgrowth of C. difficile.

C. difficile produces toxins A and B which contribute to the development of CDAD. Hypertoxin producing strains of C. difficile cause increased morbidity and mortality, as these infections can be refractory to antimicrobial therapy and may require colectomy. CDAD must be considered in all patients who present with diarrhea following antibacterial use. Careful medical history is necessary since CDAD has been reported to occur over two months after the administration of antibacterial agents.

If CDAD is suspected or confirmed, ongoing antibacterial use not directed against C. difficile may need to be discontinued. Appropriate fluid and electrolyte management, protein supplementation, antibacterial treatment of C. difficile, and surgical evaluation should be instituted as clinically indicated.

Severe Cutaneous Adverse Reactions

There have been reports of severe cutaneous adverse reactions (SCAR), such as Stevens-Johnson syndrome (SJS), toxic epidermal necrolysis (TEN), drug reaction with eosinophilia and systemic symptoms (DRESS), and acute generalized exanthematous pustulosis (AGEP) associated with MYCOBUTIN (see ADVERSE REACTIONS).

If patients develop a skin rash they should be monitored closely, and MYCOBUTIN discontinued if lesions progress. Specifically, for DRESS, a multi-system potential life-threatening SCAR, time to onset of the first symptoms may be prolonged. DRESS is a clinical diagnosis, and its clinical presentation remains the basis for decision making. An early withdrawal of MYCOBUTIN is essential because of the syndrome's mortality and visceral involvement (e.g., liver, bone marrow or kidney).

Antiretroviral and Anti-HCV Drug Interactions

Protease inhibitors act as substrates or inhibitors of CYP3A4 mediated metabolism. Therefore, due to significant drug-drug interactions between protease inhibitors and rifabutin, their concomitant use should be based on the overall assessment of the patient and a patient-specific drug profile. The concomitant use of protease inhibitors may require at least a 50% reduction in rifabutin dose, and depending on the protease inhibitor, an adjustment of the antiretroviral drug dose. Increased monitoring for adverse events is recommended when using these drug combinations (see PRECAUTIONS-Drug Interactions).

MYCOBUTIN is a CYP3A inducer. Co-administration with antiretroviral drugs metabolized by CYP3A, including but not limited to products containing bictegravir, elvitegravir, oral rilpivirine, or doravirine and anti-HCV drugs including but not limited to sofosbuvir (alone or in combination) may decrease plasma concentrations of those drugs, which may lead to loss of virologic response and possible development of resistance. Therefore, co-administration with antiretroviral and anti-HCV drugs metabolized by CYP3A is not recommended or there may be a need to increase the dose of antiretroviral or anti-HCV drugs (see PRECAUTIONS-Drug Interactions).

For further recommendations, please refer to the most recent prescribing information of the antiretrovirals or anti-HCV drugs or contact the specific manufacturer.

PRECAUTIONS

General

Because treatment with MYCOBUTIN Capsules may be associated with neutropenia, and more rarely thrombocytopenia, physicians should consider obtaining hematologic studies periodically in patients receiving prophylaxis with MYCOBUTIN.

Information for Patients

Patients should be advised of the signs and symptoms of both MAC and tuberculosis, and should be instructed to consult their physicians if they develop new complaints consistent with either of these diseases. In addition, since MYCOBUTIN may rarely be associated with myositis and uveitis, patients should be advised to notify their physicians if they develop signs or symptoms suggesting either of these disorders.

Urine, feces, saliva, sputum, perspiration, tears, and skin may be colored brown-orange with rifabutin and some of its metabolites. Soft contact lenses may be permanently stained. Patients to be treated with MYCOBUTIN should be made aware of these possibilities.

Diarrhea is a common problem caused by antibacterials which usually ends when the antibacterial is discontinued. Sometimes, after starting treatment with antibacterials, patients can develop watery and bloody stools (with or without stomach cramps and fever) even as late as two or more months after having taken the last dose of the antibacterial. If this occurs, patients should contact their physician as soon as possible.

Drug Interactions

Effect of Rifabutin on the Pharmacokinetics of Other Drugs

Rifabutin induces CYP3A enzymes and therefore may reduce the plasma concentrations of drugs metabolized by those enzymes. This effect may reduce the efficacy of standard doses of such drugs, which include itraconazole, clarithromycin, and saquinavir.

Effect of Other Drugs on Rifabutin Pharmacokinetics

Some drugs that inhibit CYP3A may significantly increase the plasma concentration of rifabutin. Therefore, carefully monitor for rifabutin associated adverse events in those patients also receiving CYP3A inhibitors, which include fluconazole and clarithromycin. In some cases, the dosage of MYCOBUTIN may need to be reduced when it is co‑administered with CYP3A inhibitors.

Table 2 summarizes the results and magnitude of the pertinent drug interactions assessed with rifabutin. The clinical relevance of these interactions and subsequent dose modifications should be judged in light of the population studied, severity of the disease, patient's drug profile, and the likely impact on the risk/benefit ratio.

Table 2 Rifabutin Interaction Studies
Co‑administered drug | Dosing regimen of co‑administered drug | Dosing regimen of rifabutin | Study population (n) | Effect on rifabutin | Effect on co‑administered drug | Recommendation
ANTIRETROVIRALS
Amprenavir | 1200 mg twice a day for 10 days | 300 mg once a day for 10 days | Healthy male subjects (6) | ↑ AUC by 193%, ↑ Cmax by 119% | ↔ | Reduce rifabutin dose by at least 50%. Monitor closely for adverse reactions.
Atazanavir/ Ritonavir | 300/100 mg once daily | 150 mg twice weekly | Healthy adult subjects | 48% ↑ in AUC, 149% ↑ Cmax of rifabutin.; 990% ↑ in AUC, 677% ↑ Cmax of 25-O‑desacetyl-rifabutin. | No significant change in pharmacokinetics. | A reduction in the dose of rifabutin (to 150 mg every other day or 3 times a week) is recommended. Increased monitoring for adverse reactions is warranted.
Bictegravir | 75 mg once a day | 300 mg once a day (fasted) | Healthy subjects | ND | ↓ AUC 38% ↓ Cmin 56% ↓ Cmax 20% | Co-administration of rifabutin with Biktarvy (bictegravir/emtricitabine/tenofovir alafenamide) is not recommended due to an expected decrease in tenofovir alafenamide in addition to the reported reduction in bictegravir. Refer to Biktarvy prescribing information for additional information.
Darunavir/Ritonavir | 600/100 mg twice a day for 12 days | 150 mg every other day for 12 days | Healthy HIV- negative adults | No significant change in rifabutin pharmacokinetics.; 881% ↑ in AUC, 377% ↑ Cmax of 25-O-desacetyl-rifabutin. | 57% ↑ in AUC, 42% ↑ Cmax of darunavir.; 66% ↑ in AUC, 68% ↑ Cmax of ritonavir. | A reduction in the dose of rifabutin (to 150 mg every other day or 3 times a week) is recommended. Increased monitoring for adverse reactions is warranted.
Delavirdine | 400 mg three times a day | 300 mg once a day | HIV-infected patients (7) | ↑ AUC by 230%, ↑ Cmax by 128% | ↓ AUC by 80%, ↓ Cmax by 75%, ↓ Cmin by 17% | CONTRAINDICATED
Didanosine | 167 or 250 mg twice a day for 12 days | 300 or 600 mg once a day for 12 days | HIV-infected patients (11) | ↔ | ↔
Dolutegravir | 50 mg daily for 14 days | 300 mg daily for 14 days | Healthy adult subjects | ND | No significant change in dolutegravir pharmacokinetics at steady state.
Doravirine | 100 mg single dose | 300 mg once a day for 16 days | Healthy subjects (12) | ND | ↓ 50% in AUC, ↓ 68% in C24 ↔ in Cmax | If concomitant use is necessary, increase the doravirine dosage as instructed in doravirine-containing product prescribing information.
Elvitegravir/ Cobicistat | 150/50 mg daily | 300 mg daily; Or 150 mg every other day | Healthy subjects (12) | No significant change in rifabutin pharmacokinetics.; 6.3-fold ↑ in AUC, 4.8-fold ↑ Cmax of 25‑O‑desacetyl-rifabutin. | No change in elvitegravir except 67% ↓ Ctrough of elvitegravir.; No change in cobicistat exposure. | Co-administration of rifabutin with elvitegravir/ cobicistat is not recommended due to an expected decrease in elvitegravir exposure.
Etravirine | 800 mg twice daily for 21 days | 300 mg daily on days 8 to 21 | Healthy volunteers (18) | No significant change in rifabutin pharmacokinetics. | 37% ↓ in AUC, 37% ↓ in Cmax and 35% ↓ in Cmin | No dose adjustment of rifabutin is required when etravirine is not co-administered with protease inhibitor/ritonavir.; Rifabutin should not be co-administered with etravirine and boosted PIs due to potential for decreased effectiveness of etravirine.
Fosamprenavir/ ritonavir | 700 mg twice a day plus ritonavir 100 mg twice a day for 2 weeks | 150 mg every other day for 2 weeks | Healthy subjects (15) | ↔ AUC [compared to rifabutin 300 mg once a day alone] ↓ Cmax by 15% | ↑ AUC by 35% [compared to historical control (fosamprenavir/ritonavir 700/100 mg twice a day)] , ↑ Cmax by 36%, ↑ Cmin by 36% | Reduce rifabutin dose by at least 75% (to a maximum 150 mg every other day or three times per week) when given with fosamprenavir/ritonavir combination.
Indinavir | 800 mg three times a day for 10 days | 300 mg once a day for 10 days | Healthy subjects (10) | ↑ AUC by 173%, ↑ Cmax by 134% | ↓ AUC by 34%, ↓ Cmax by 25%, ↓ Cmin by 39% | Reduce rifabutin dose by 50%, and increase indinavir dose from 800 mg to 1000 mg three times a day.
Lopinavir/ ritonavir | 400/100 mg twice a day for 20 days | 150 mg once a day for 10 days | Healthy subjects (14) | ↑ AUC by 203% [also taking zidovudine 500 mg once a day] ↓ Cmax by 112% | ↔ | Reduce rifabutin dose by at least 75% (to a maximum 150 mg every other day or three times per week) when given with lopinavir/ritonavir combination. Monitor closely for adverse reactions. Reduce rifabutin dosage further, as needed.
Saquinavir/ ritonavir | 1000/100 mg twice a day for 14 or 22 days | 150 mg every 3 days for 21–22 days | Healthy subjects | ↑ AUC by 53% [compared to rifabutin 150 mg once a day alone] ↑ Cmax by 88% (n=11) | ↓ AUC by 13%, ↓ Cmax by 15%, (n=19) | Reduce rifabutin dose by at least 75% (to a maximum 150 mg every other day or three times per week) when given with saquinavir/ritonavir combination. Monitor closely for adverse reactions.
Rilpivirine | 25 mg once a day | 300 mg once a day | Healthy subjects (18) | ND | ↓ AUC by 42% ↓ Cmin by 48% ↓ Cmax by 31% | Co-administration of rifabutin with Odefsey (rilpivirine/tenofovir alafenamide/emtricitabine) is not recommended, due to an expected decrease in tenofovir alafenamide in addition to the reported reduction in rilpivirine. Refer to Odefsey prescribing information for additional information.; Co-administration of rifabutin with cabotegravir/rilpivirine prolonged-release injectable suspension is contraindicated.
Ritonavir | 500 mg twice a day for 10 days | 150 mg once a day for 16 days | Healthy subjects (5) | ↑ AUC by 300%, ↑ Cmax by 150% | ND | Reduce rifabutin dose by at least 75% (to a maximum 150 mg every other day or three times per week) when given with lopinavir/ritonavir combination. Monitor closely for adverse reactions. Reduce rifabutin dosage further, as needed.
Tipranavir/ ritonavir | 500/200 twice a day for 15 doses | 150 mg single dose | Healthy subjects (20) | ↑ AUC by 190%, ↑ Cmax by 70% | ↔ | Reduce rifabutin dose by at least 75% (to a maximum 150 mg every other day or three times per week) when given with tipranavir/ritonavir combination. Monitor closely for adverse reactions. Reduce rifabutin dosage further, as needed.
Nelfinavir | 1250 mg twice a day for 7–8 days | 150 mg once a day for 8 days | HIV-infected patients (11) | ↑ AUC by 83%, [compared to rifabutin 300 mg once a day alone] ↑ Cmax by 19% | ↔ | Reduce rifabutin dose by 50% (to 150 mg once a day) and increase the nelfinavir dose to 1250 mg twice a day.
Zidovudine | 100 or 200 mg every four hours | 300 or 450 mg once a day | HIV-infected patients (16) | ↔ | ↓ AUC by 32%, ↓ Cmax by 48%, | Because zidovudine levels remained within the therapeutic range during co-administration of rifabutin, dosage adjustments are not necessary.
ANTI-HCV DRUGS
Sofosbuvir | 400 mg on day 1 and day 21 | 300 mg daily on day 10 to day 29 | Healthy subjects (20) | ND | 36% ↓ in Cmax and 24% ↓ AUC | Co-administration of rifabutin with sofosbuvir (alone or in combination) is not recommended.
ANTIFUNGALS
Fluconazole | 200 mg once a day for 2 weeks | 300 mg once a day for 2 weeks | HIV-infected patients (12) | ↑ AUC by 82%, ↑ Cmax by 88% | ↔ | Monitor for rifabutin associated adverse events. Reduce rifabutin dose or suspend MYCOBUTIN use if toxicity is suspected.
Posaconazole | 200 mg once a day for 10 days | 300 mg once a day for 17 days | Healthy subjects (8) | ↑ AUC by 72%, ↑ Cmax by 31% | ↓ AUC by 49%, ↓ Cmax by 43% | If co-administration of these two drugs cannot be avoided, patients should be monitored for adverse events associated with rifabutin administration, and lack of posaconazole efficacy.
Itraconazole | 200 mg once a day | 300 mg once a day | HIV-Infected patients (6) | ↑ [data from a case report] | ↓ AUC by 70%, ↓ Cmax by 75%, | If co-administration of these two drugs cannot be avoided, patients should be monitored for adverse events associated with rifabutin administration, and lack of itraconazole efficacy. In a separate study, one case of uveitis was associated with increased serum rifabutin levels following co-administration of rifabutin (300 mg once a day) with itraconazole (600–900 mg once a day).
Voriconazole | 400 mg twice a day for 7 days (maintenance dose) | 300 mg once a day for 7 days | Healthy male subjects (12) | ↑ AUC by 331%, ↑ Cmax by 195% | ↑ AUC by ~100%, ↑ Cmax by ~100% [compared to voriconazole 200 mg twice a day alone] | CONTRAINDICATED
ANTI-PCP (Pneumocystis carinii pneumonia)
Dapsone | 50 mg once a day | 300 mg once a day | HIV-infected patients (16) | ND | ↓ AUC by 27–40%
Sulfamethoxazole-Trimethoprim | 800/160 mg | 300 mg once a day | HIV-infected patients (12) | ↔ | ↓ AUC by 15–20%
ANTI-MAC (Mycobacterium avium intracellulare complex)
Azithromycin | 500 mg once a day for 1 day, then 250 mg once a day for 9 days | 300 mg once a day | Healthy subjects (6) | ↔ | ↔
Clarithromycin | 500 mg twice a day | 300 mg once a day | HIV-infected patients (12) | ↑ AUC by 75% | ↓ AUC by 50% | Monitor for rifabutin associated adverse events. Reduce dose or suspend use of MYCOBUTIN if toxicity is suspected. Alternative treatment for clarithromycin should be considered when treating patients receiving rifabutin
ANTI-TB (Tuberculosis)
Ethambutol | 1200 mg | 300 mg once a day for 7 days | Healthy subjects (10) | ND | ↔
Isoniazid | 300 mg | 300 mg once a day for 7 days | Healthy subjects (6) | ND | ↔
Bedaquiline | 400 mg daily on day 1 and day 29 | 300 mg daily | Healthy subjects (17) | ND | No change in bedaquiline pharmacokinetics.; 1.4-fold ↑ in M2 and approximately 3.0-fold ↑ in M3 metabolites of bedaquiline. | Avoid bedaquiline co-administration with rifabutin due to the adverse reactions associated with increased bedaquiline metabolite concentrations.
OTHER
Methadone | 20 – 100 mg once a day | 300 mg once a day for 13 days | HIV-infected patients (24) | ND | ↔
Ethinylestradiol (EE)/Norethindrone (NE) | 35 mg EE / 1 mg NE for 21 days | 300 mg once a day for 10 days | Healthy female subjects (22) | ND | EE: ↓ AUC by 35%, ↓ Cmax by 20% NE: ↓ AUC by 46% | Patients should be advised to use additional or alternative methods of contraception.
Theophylline | 5 mg/kg | 300 mg for 14 days | Healthy subjects (11) | ND | ↔
↑ indicates increase; ↓ indicates decrease; ↔ indicates no significant change
ND - No Data
AUC - Area under the Concentration vs. Time Curve; Cmax - Maximum serum concentration; Cmin – Minimum serum concentration

Other drugs

The structurally similar drug, rifampin, is known to reduce the plasma concentrations of a number of other drugs (see prescribing information for rifampin). Although a weaker enzyme inducer than rifampin, rifabutin may be expected to have some effect on those drugs as well.

Carcinogenesis, Mutagenesis, Impairment of Fertility

Long-term carcinogenicity studies were conducted with rifabutin in mice and in rats. Rifabutin was not carcinogenic in mice at doses up to 180 mg/kg/day, or approximately 36 times the recommended human daily dose. Rifabutin was not carcinogenic in the rat at doses up to 60 mg/kg/day, about 12 times the recommended human dose.

Rifabutin was not mutagenic in the bacterial mutation assay (Ames Test) using both rifabutin-susceptible and resistant strains. Rifabutin was not mutagenic in Schizosaccharomyces pombe P1 and was not genotoxic in V-79 Chinese hamster cells, human lymphocytes in vitro, or mouse bone marrow cells in vivo.

Fertility was impaired in male rats given 160 mg/kg (32 times the recommended human daily dose).

Pregnancy

Rifabutin should be used in pregnant women only if the potential benefit justifies the potential risk to the fetus. There are no adequate and well-controlled studies in pregnant or breastfeeding women.

Reproduction studies have been carried out in rats and rabbits given rifabutin using dose levels up to 200 mg/kg (about 6 to 13 times the recommended human daily dose based on body surface area comparisons). No teratogenicity was observed in either species. In rats, given 200 mg/kg/day, (about 6 times the recommended human daily dose based on body surface area comparisons), there was a decrease in fetal viability. In rats, at 40 mg/kg/day (approximately equivalent to the recommended human daily dose based on body surface area comparisons), rifabutin caused an increase in fetal skeletal variants. In rabbits, at 80 mg/kg/day (about 5 times the recommended human daily dose based on body surface area comparisons), rifabutin caused maternotoxicity and increase in fetal skeletal anomalies. Because animal reproduction studies are not always predictive of human response, rifabutin should be used in pregnant women only if the potential benefit justifies the potential risk to the fetus.

Nursing Mothers

It is not known whether rifabutin is excreted in human milk. Because many drugs are excreted in human milk and because of the potential for serious adverse reactions in nursing infants, a decision should be made whether to discontinue nursing or discontinue the drug, taking into account the importance of the drug to the mother.

Pediatric Use

Safety and effectiveness of rifabutin for prophylaxis of MAC in children have not been established. Limited safety data are available from treatment use in 22 HIV-positive children with MAC who received MYCOBUTIN in combination with at least two other antimycobacterials for periods from 1 to 183 weeks. Mean doses (mg/kg) for these children were: 18.5 (range 15.0 to 25.0) for infants 1 year of age, 8.6 (range 4.4 to 18.8) for children 2 to 10 years of age, and 4.0 (range 2.8 to 5.4) for adolescents 14 to 16 years of age. There is no evidence that doses greater than 5 mg/kg daily are useful. Adverse experiences were similar to those observed in the adult population, and included leukopenia, neutropenia, and rash. In addition, corneal deposits have been observed in some patients during routine ophthalmologic surveillance of HIV-positive pediatric patients receiving MYCOBUTIN as part of a multiple-drug regimen for MAC prophylaxis. These are tiny, almost transparent, asymptomatic peripheral and central corneal deposits which do not impair vision.

Geriatric Use

Clinical studies of MYCOBUTIN did not include sufficient numbers of subjects aged 65 and over to determine whether they respond differently from younger subjects. Other reported clinical experience has not identified differences in responses between the elderly and younger patients. In general, dose selection for an elderly patient should be cautious, usually starting at the low end of the dosing range, reflecting the greater frequency of decreased hepatic, renal, or cardiac function, and of concomitant disease or other drug therapy (see CLINICAL PHARMACOLOGY).

ADVERSE REACTIONS

Adverse Reactions from Clinical Trials

MYCOBUTIN Capsules were generally well tolerated in the controlled clinical trials. Discontinuation of therapy due to an adverse event was required in 16% of patients receiving MYCOBUTIN, compared to 8% of patients receiving placebo in these trials. Primary reasons for discontinuation of MYCOBUTIN were rash (4% of treated patients), gastrointestinal intolerance (3%), and neutropenia (2%).

The following table enumerates adverse experiences that occurred at a frequency of 1% or greater, among the patients treated with MYCOBUTIN in studies 023 and 027.

Table 3 Clinical Adverse Experiences Reported in ≥1% of Patients Treated With MYCOBUTIN
Adverse event | MYCOBUTIN (n = 566) % | Placebo (n = 580) %
Body as a whole
Abdominal pain | 4 | 3
Asthenia | 1 | 1
Chest pain | 1 | 1
Fever | 2 | 1
Headache | 3 | 5
Pain | 1 | 2
Blood and lymphatic system
Leucopenia | 10 | 7
Anemia | 1 | 2
Digestive System
Anorexia | 2 | 2
Diarrhea | 3 | 3
Dyspepsia | 3 | 1
Eructation | 3 | 1
Flatulence | 2 | 1
Nausea | 6 | 5
Nausea and vomiting | 3 | 2
Vomiting | 1 | 1
Musculoskeletal system
Myalgia | 2 | 1
Nervous system
Insomnia | 1 | 1
Skin and appendages
Rash | 11 | 8
Special senses
Taste perversion | 3 | 1
Urogenital system
Discolored urine | 30 | 6

CLINICAL ADVERSE EVENTS REPORTED IN <1% OF PATIENTS WHO RECEIVED MYCOBUTIN

Considering data from the 023 and 027 pivotal trials, and from other clinical studies, MYCOBUTIN appears to be a likely cause of the following adverse events which occurred in less than 1% of treated patients: flu-like syndrome, hepatitis, hemolysis, arthralgia, myositis, chest pressure or pain with dyspnea, skin discoloration, thrombocytopenia, pancytopenia and jaundice.

The following adverse events have occurred in more than one patient receiving MYCOBUTIN, but an etiologic role has not been established: seizure, paresthesia, aphasia, confusion, and non-specific T wave changes on electrocardiogram.

When MYCOBUTIN was administered at doses from 1050 mg/day to 2400 mg/day, generalized arthralgia and uveitis were reported. These adverse experiences abated when MYCOBUTIN was discontinued.

Mild to severe, reversible uveitis has been reported less frequently when MYCOBUTIN is used at 300 mg as monotherapy in MAC prophylaxis versus MYCOBUTIN in combination with clarithromycin for MAC treatment (see also WARNINGS).

Uveitis has been infrequently reported when MYCOBUTIN is used at 300 mg/day as monotherapy in MAC prophylaxis of HIV-infected persons, even with the concomitant use of fluconazole and/or macrolide antibacterials. However, if higher doses of MYCOBUTIN are administered in combination with these agents, the incidence of uveitis is higher.

Patients who developed uveitis had mild to severe symptoms that resolved after treatment with corticosteroids and/or mydriatic eye drops; in some severe cases, however, resolution of symptoms occurred after several weeks.

When uveitis occurs, temporary discontinuance of MYCOBUTIN and ophthalmologic evaluation are recommended. In most mild cases, MYCOBUTIN may be restarted; however, if signs or symptoms recur, use of MYCOBUTIN should be discontinued (Morbidity and Mortality Weekly Report, September 9, 1994).

Corneal deposits have been reported during routine ophthalmologic surveillance of some HIV-positive pediatric patients receiving MYCOBUTIN as part of a multiple drug regimen for MAC prophylaxis. The deposits are tiny, almost transparent, asymptomatic peripheral and central corneal deposits, and do not impair vision.

The following table enumerates the changes in laboratory values that were considered as laboratory abnormalities in Studies 023 and 027.

Table 4 Percentage of Patients With Laboratory Abnormalities
Laboratory abnormalities | MYCOBUTIN (n = 566) % | PLACEBO (n = 580) %
Chemistry
Increased alkaline phosphatase [All values >450 U/L] | <1 | 3
Increased SGOT [All values >150 U/L] | 7 | 12
Increased SGPT | 9 | 11
Hematology
Anemia [All hemoglobin values <8.0 g/dL] | 6 | 7
Eosinophilia | 1 | 1
Leukopenia [All WBC values <1,500/mm^3] | 17 | 16
Neutropenia [All ANC values <750/mm^3] | 25 | 20
Thrombocytopenia [All platelet count values <50,000/mm^3] | 5 | 4
Includes grades 3 or 4 toxicities as specified:

The incidence of neutropenia in patients treated with MYCOBUTIN was significantly greater than in patients treated with placebo (p = 0.03). Although thrombocytopenia was not significantly more common among patients treated with MYCOBUTIN in these trials, MYCOBUTIN has been clearly linked to thrombocytopenia in rare cases. One patient in Study 023 developed thrombotic thrombocytopenic purpura, which was attributed to MYCOBUTIN.

Adverse Reactions from Post-Marketing Experience

Adverse reactions identified through post-marketing surveillance by system organ class (SOC) are listed below:

Blood and lymphatic system disorders: White blood cell disorders (including agranulocytosis, lymphopenia, granulocytopenia, neutropenia, white blood cell count decreased, neutrophil count decreased), platelet count decreased.

Immune system disorders: Hypersensitivity, bronchospasm, rash, and eosinophilia.

Gastrointestinal disorders: Clostridioides difficile colitis/Clostridioides difficile associated diarrhea.

Pyrexia, rash and other hypersensitivity reactions such as eosinophilia and bronchospasm might occur, as has been seen with other antibacterials.

A limited occurrence of skin discoloration has been reported.

Severe cutaneous adverse reactions (SCARs)

MYCOBUTIN has been associated with the occurrence of DRESS as well as other SCARs such as SJS, TEN, and AGEP (see WARNINGS).

Rifamycin hypersensitivity reactions

Hypersensitivity to rifamycins have been reported including flu-like symptoms, bronchospasm, hypotension, urticaria, angioedema, conjunctivitis, thrombocytopenia or neutropenia.

ANIMAL TOXICOLOGY

Liver abnormalities (increased bilirubin and liver weight) occurred in mice, rats and monkeys at doses (respectively) 0.5, 1, and 3 times the recommended human daily dose based on body surface area comparisons. Testicular atrophy occurred in baboons at doses 2 times the recommended human dose based on body surface area comparisons, and in rats at doses 6 times the recommended human daily dose based on body surface area comparisons.

OVERDOSAGE

No information is available on accidental overdosage in humans.

Treatment

While there is no experience in the treatment of overdose with MYCOBUTIN Capsules, clinical experience with rifamycins suggests that gastric lavage to evacuate gastric contents (within a few hours of overdose), followed by instillation of an activated charcoal slurry into the stomach, may help absorb any remaining drug from the gastrointestinal tract.

Rifabutin is 85% protein bound and distributed extensively into tissues (Vss:8 to 9 L/kg). It is not primarily excreted via the urinary route (less than 10% as unchanged drug); therefore, neither hemodialysis nor forced diuresis is expected to enhance the systemic elimination of unchanged rifabutin from the body in a patient with an overdose of MYCOBUTIN.

DOSAGE AND ADMINISTRATION

It is recommended that MYCOBUTIN Capsules be administered at a dose of 300 mg once daily. For those patients with propensity to nausea, vomiting, or other gastrointestinal upset, administration of MYCOBUTIN at doses of 150 mg twice daily taken with food may be useful. Doses of MYCOBUTIN may be administered mixed with foods such as applesauce.

For patients with severe renal impairment (creatinine clearance less than 30 mL/min), consider reducing the dose of MYCOBUTIN by 50%, if toxicity is suspected. No dosage adjustment is required for patients with mild to moderate renal impairment. Reduction of the dose of MYCOBUTIN may also be needed for patients receiving concomitant treatment with certain other drugs (see PRECAUTIONS-Drug Interactions).

Mild hepatic impairment does not require a dose modification. The pharmacokinetics of rifabutin in patients with moderate and severe hepatic impairment is not known.

HOW SUPPLIED

MYCOBUTIN (rifabutin) Capsules, USP are supplied as hard gelatin capsules having an opaque red-brown cap and body, imprinted with MYCOBUTIN/PHARMACIA & UPJOHN in white ink, each containing 150 mg of rifabutin, USP.

MYCOBUTIN is available as follows:

NDC 0013-5301-17 Bottles of 100 capsules

STORAGE AND HANDLING

Keep tightly closed and dispense in a tight container as defined in the USP. Store at 25°C (77°F); excursions permitted to 15°–30°C (59°–86°F) [see USP Controlled Room Temperature].

LAB-0217-12.0
Revised 11/2024

PRINCIPAL DISPLAY PANEL - 150 mg Capsule Bottle Label

Pfizer
NDC 0013-5301-17

Mycobutin®
(rifabutin) capsules, USP

150 mg

100 Capsules
Rx only